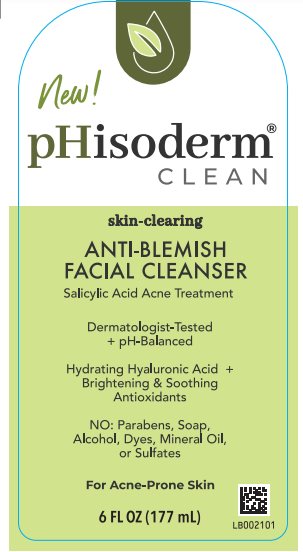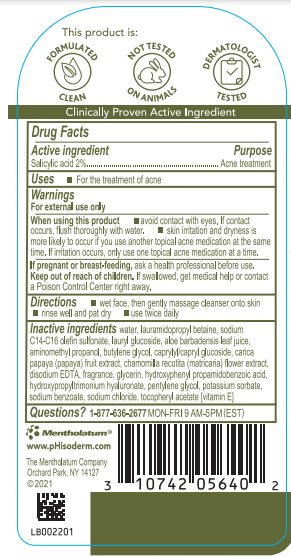 DRUG LABEL: pHisoderm
NDC: 10742-1235 | Form: GEL
Manufacturer: The Mentholatum Company
Category: otc | Type: HUMAN OTC DRUG LABEL
Date: 20241213

ACTIVE INGREDIENTS: SALICYLIC ACID 20 mg/1 mL
INACTIVE INGREDIENTS: GLYCERIN; HYDROXYPHENYL PROPAMIDOBENZOIC ACID; DIHYDROXYPROPYLTRIMONIUM; PENTYLENE GLYCOL; POTASSIUM SORBATE; SODIUM BENZOATE; SODIUM CHLORIDE; .ALPHA.-TOCOPHEROL ACETATE; WATER; LAURAMIDOPROPYL BETAINE; SODIUM C14-16 OLEFIN SULFONATE; LAURYL GLUCOSIDE; ALOE VERA LEAF; AMINOMETHYLPROPANOL; BUTYLENE GLYCOL; CAPRYLYL/CAPRYL OLIGOGLUCOSIDE; PAPAYA; CHAMOMILE; EDETATE DISODIUM

Drug Facts - pHisoderm Clean Anti-Blemish Facial Cleanser

Active ingredient

Salicylic acid 2%

Purpose

Acne treatment

Uses

- For the treatment of acne

Warnings

For external use only

When using this product

- avoid contact with eyes. If contact occurs, flush thoroughly with water.
- skin irritation and dryness is more likely to occur if you use another topical acne medication at the same time. If irritation occurs, only use one topical acne medication at a time.

If pregnant or breast-feeding,

ask a health professional before use.

Keep out of reach of children.

If swallowed, get medical help or contact a Poison Control Center right away.

Directions

- wet face, then gently massage cleanser onto skin
- rinse well and pat dry
- use twice daily

Inactive ingredients

water, lauramidopropyl betaine, sodium C14-16 olefin sulfonate, lauryl glucoside, aloe barbadensis leaf juice, aminomethyl propanol, butylene glycol, caprylyl/capryl glucoside, carica papaya (papaya) fruit extract, chamomilla recutita (matricaria) flower extract, disodium EDTA, fragrance, glycerin, hydroxyphenyl propamidobenzoic acid, hydroxypropyltrimonium hyaluronate, pentylene glycol, potassium sorbate, sodium benzoate, sodium chloride, tocopheryl acetate [vitamin E]

Questions?

1-877-636-2677 MON-FRI 9 AM to 5 PM (EST)